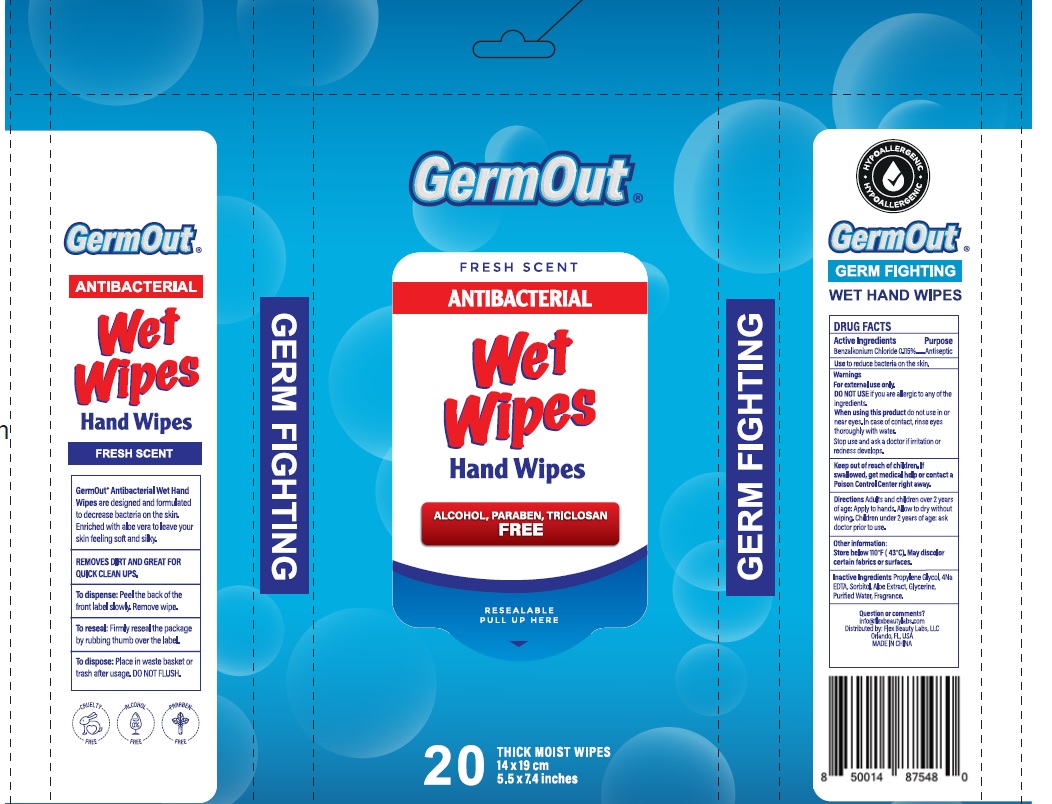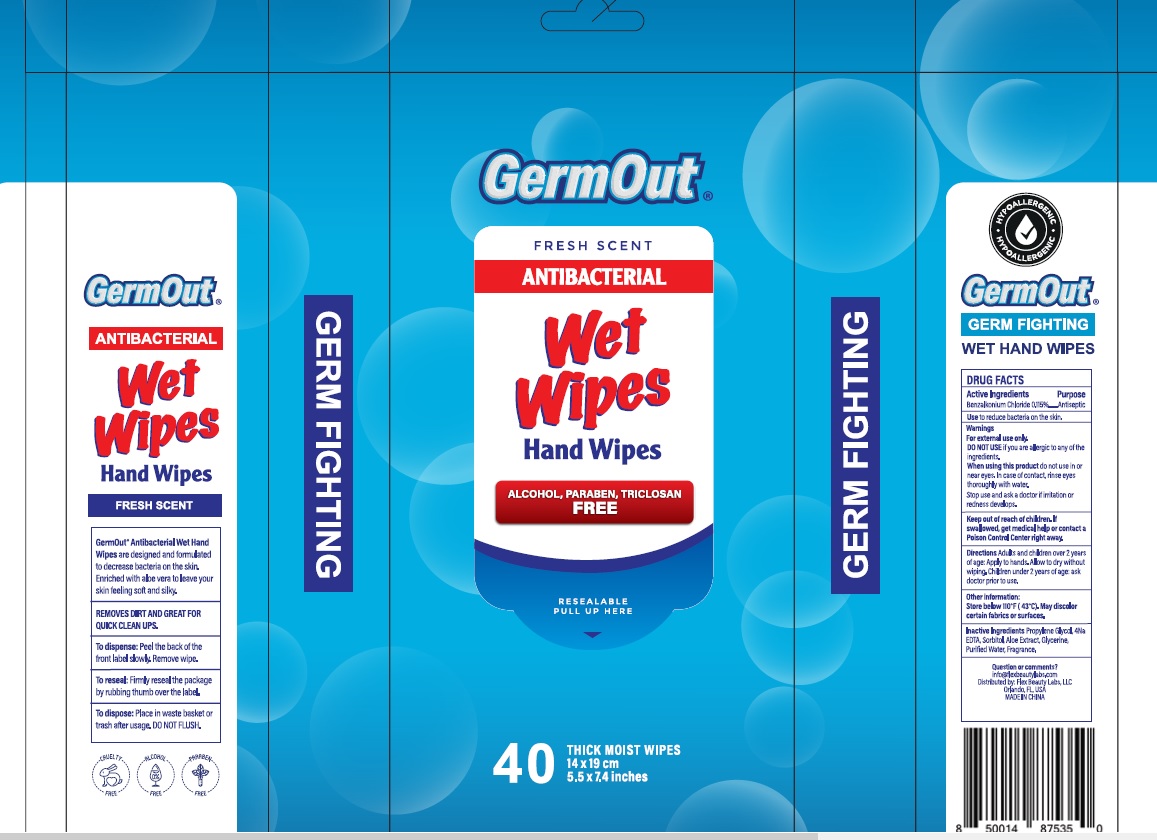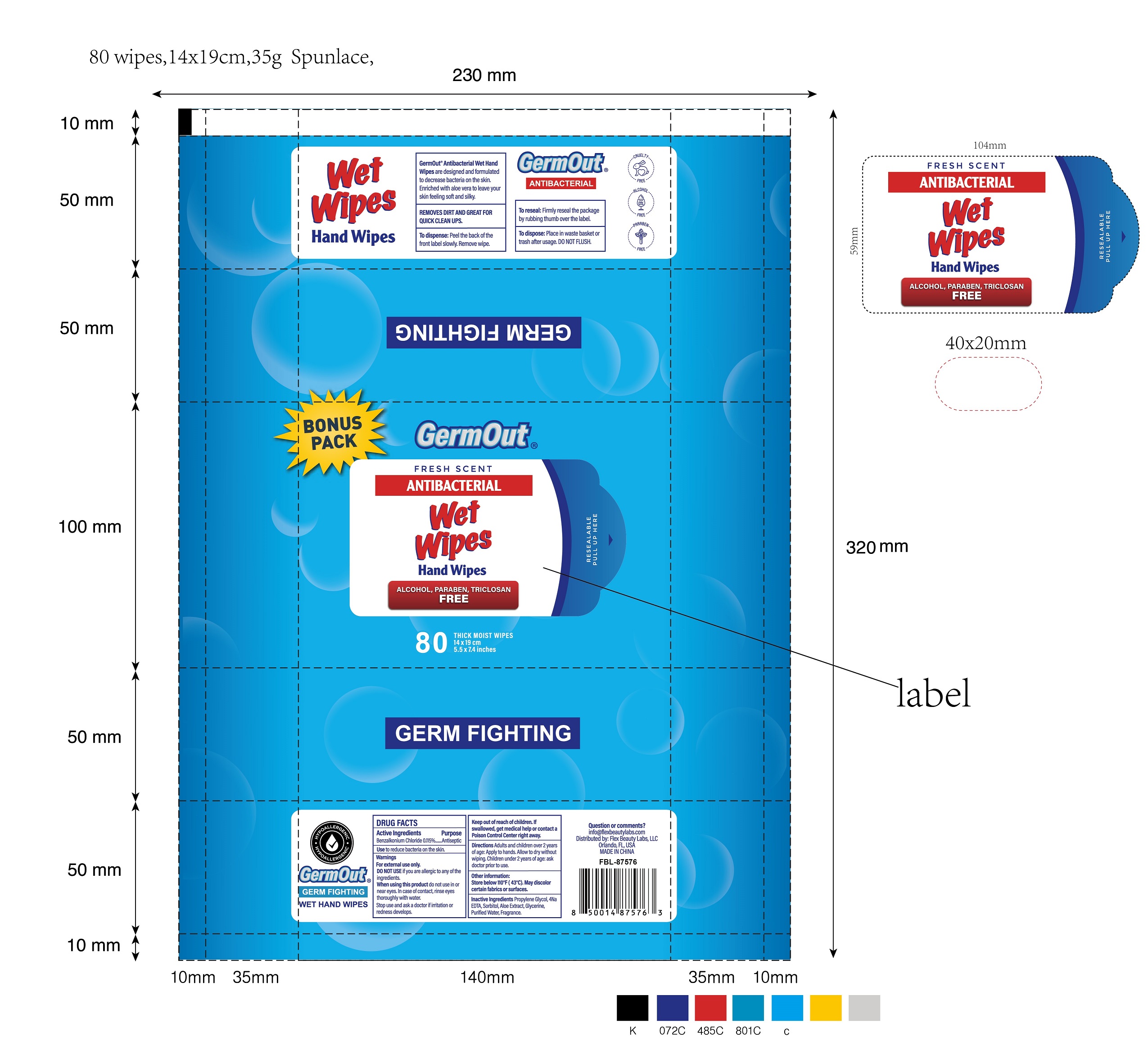 DRUG LABEL: Antiseptic Wipes
NDC: 72308-028 | Form: CLOTH
Manufacturer: Flex Beauty Labs
Category: otc | Type: HUMAN OTC DRUG LABEL
Date: 20200804

ACTIVE INGREDIENTS: BENZALKONIUM CHLORIDE 0.115 mg/100 mg
INACTIVE INGREDIENTS: WATER; GLYCERIN; PROPYLENE GLYCOL; ALOE VERA LEAF; SORBITOL; EDETATE SODIUM; ETHYLHEXYLGLYCERIN

Germout- Wet Wipes Antibaterial

Active ingredients

Benalkonium chloride (0.115%)

Purpose

Antiseptic

Use

Use to reduce bacteria on the skin

Warnings

For external use only

Do not use if you are allegic to any of the ingredients.

When using this product do not use in or near eyes.

In cases of contact, rinse eyes thoroughly with water.

Stop use and ask a doctor if irritation or redness develops.

Keep out of reach of children.

If swallowed, get medical help or contact a Poison Control Center right away

Directions:

- Adults and children over 2 yeas of age:Apply to hands. Allow to dry without wioing.
- Children under 2 year of age:ask doctor prior to use

Other information

store below 110°F (43°C) May discolor certain fabrics or surfaces.

Inactive ingredients

Water, Glycerin, Aloe barbadensis leaf juice, Fragrance, 4Na EDTA,Propylene Glycol. sorbito